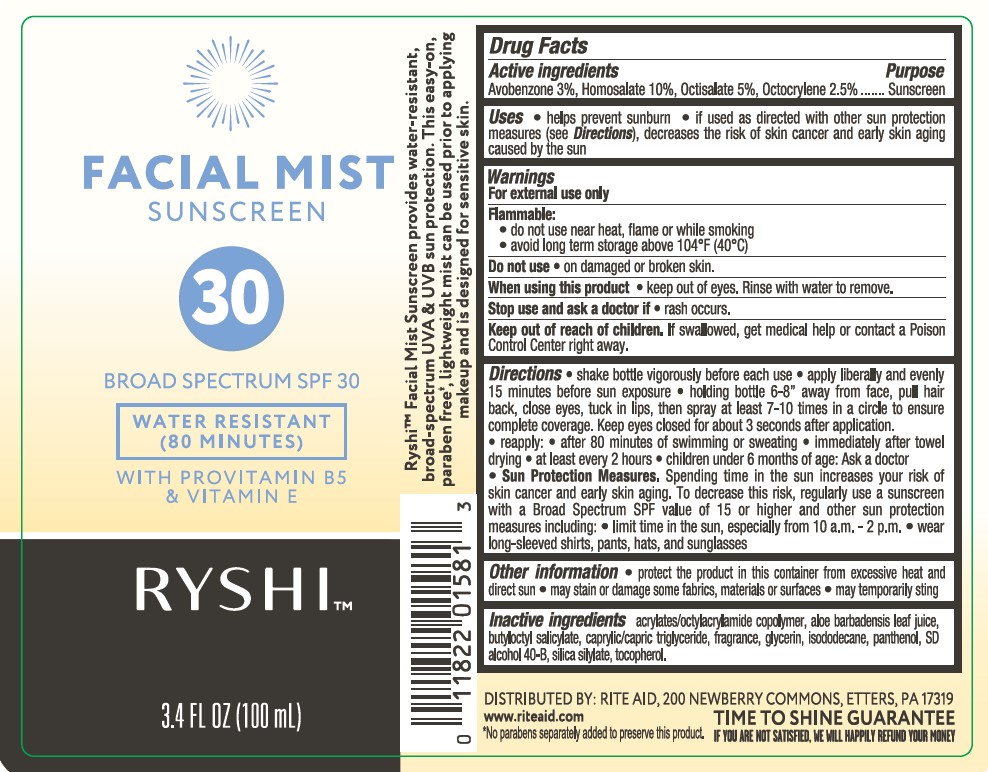 DRUG LABEL: Rite Aid Ryshi Facial Mist Sunscreen Broad Spectrum SPF 30
NDC: 11822-0026 | Form: SPRAY
Manufacturer: Rite Aid
Category: otc | Type: HUMAN OTC DRUG LABEL
Date: 20231115

ACTIVE INGREDIENTS: AVOBENZONE 30 mg/1 mL; HOMOSALATE 100 mg/1 mL; OCTISALATE 50 mg/1 mL; OCTOCRYLENE 25 mg/1 mL
INACTIVE INGREDIENTS: ALCOHOL; ACRYLATE/ISOBUTYL METHACRYLATE/N-TERT-OCTYLACRYLAMIDE COPOLYMER (75000 MW); ALOE VERA LEAF; .ALPHA.-TOCOPHEROL, DL-; GLYCERIN; MEDIUM-CHAIN TRIGLYCERIDES; BUTYLOCTYL SALICYLATE; PANTHENOL; ISODODECANE

Rite Aid Ryshi Facial Mist Sunscreen Broad Spectrum SPF 30

Active ingredients

Avobenzone 3.0%, Homosalate 10.0%, Octisalate 5.0%, Octocrylene 2.5%

Purpose

Sunscreen

Uses

- helps prevent sunburn
- if used as directed with other sun protection measures (see Directions), decreases the risk of skin cancer and early skin aging caused by the sun

Warnings

For external use only

FLAMMABLE:

• do not use near heat, flame or while smoking

• avoid long term storage above 104°F (40°C)

Do not use

• on damaged or broken skin.

When using this product

• keep out of eyes. Rinse with water to remove.

Stop use and ask a doctor if

• rash occurs.

Keep out of reach of children.

If swallowed, get medical help or contact a Poison Control Center right away.

Directions

- shake bottle vigorously before each use.
- apply liberally and evenly 15 minutes before sun exposure.
- hold bottle 6-8 inches away from face, pull hair back, close eyes, tuck lips, then spray at least 7-10 times in a circle to ensure complete coverage. Keep eyes closed for about 3 seconds after application.
- reapply:

• after 80 minutes of swimming or sweating

• immediately after towel drying

• at least every 2 hours

- children under 6 months of age: Ask a doctor
- Sun Protection Measures. Spending time in the sun increases your risk of skin cancer and early skin aging. To decrease this risk, regularly use a sunscreen with a Broad Spectrum SPF value of 15 or higher and other sun protection measures including:

• limit time in the sun, especially from 10 a.m. - 2 p.m.

• wear long-sleeved shirts, pants, hats, and sunglasses

Other information

- protect the product in this container from excessive heat and direct sun
- may stain or damage some fabrics, materials or surfaces
- may temporarily sting

Inactive ingredients

acrylates/octylacrylamide copolymer, aloe barbadensis leaf juice, butyloctyl salicylate, caprylic/capric triglyceride, fragrance, glycerin, isododecane, panthenol, SD alcohol 40-B, silica silylate, tocopherol.